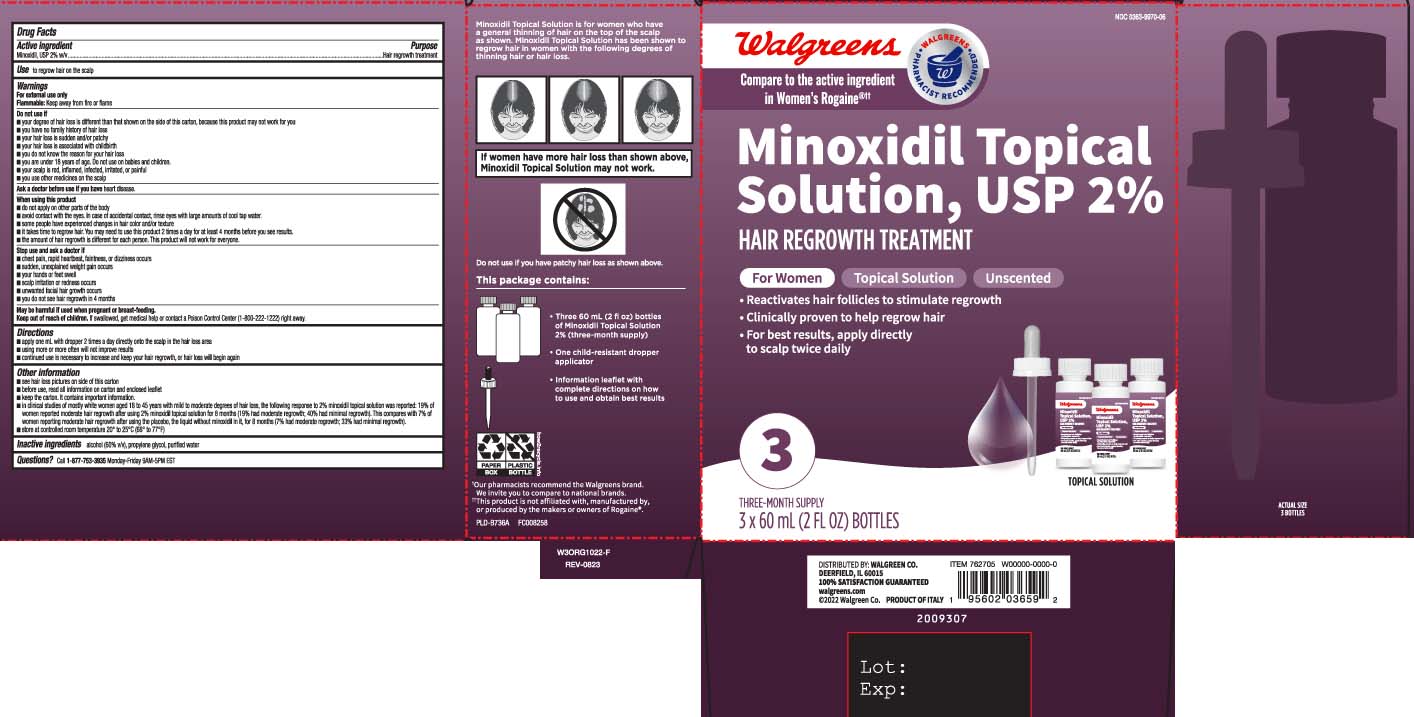 DRUG LABEL: Minoxidil
NDC: 0363-9970 | Form: SOLUTION
Manufacturer: Walgreens
Category: otc | Type: HUMAN OTC DRUG LABEL
Date: 20250521

ACTIVE INGREDIENTS: MINOXIDIL 2 g/100 mL
INACTIVE INGREDIENTS: ALCOHOL; PROPYLENE GLYCOL; WATER

Minoxidil Topical Solution for Women

Active ingredient

Minoxidil, USP 2% w/v

Purpose

Hair regrowth treatment

Use

to regrow hair on the scalp

Warnings

For external use only
Flammable: Keep away from fire or flame

Do not use if

- your degree of hair loss is different than that shown on the side of this carton, because this product may not work for you
- you have no family history of hair loss
- your hair loss is sudden and/or patchy
- your hair loss is associated with childbirth
- you do not know the reason for your hair loss
- you are under 18 years of age. Do not use on babies and children.
- your scalp is red, inflamed, infected, irritated, or painful
- you use other medicines on the scalp

Ask a doctor before use if you have

heart disease

When using this product

- do not apply on other parts of the body
- avoid contact with the eyes. In case of accidental contact, rinse eyes with large amounts of cool tap water.
- some people have experienced changes in hair color and/or texture
- it takes time to regrow hair. You may need to use this product 2 times a day for at least 4 months before you see results.
- the amount of hair regrowth is different for each person. This product will not work for everyone.

Stop use and ask a doctor if

- chest pain, rapid heartbeat, faintness, or dizziness occurs
- sudden, unexplained weight gain occurs
- your hands or feet swell
- scalp irritation or redness occurs
- unwanted facial hair growth occurs
- you do not see hair regrowth in 4 months

Keep out of reach of children.

If swallowed, get medical help or contact a Poison Control Center (1-800-222-1222) right away.

Directions

- apply one mL with dropper 2 times a day directly onto the scalp in the hair loss area
- using more or more often will not improve results
- continued use is necessary to increase and keep your hair regrowth, or hair loss will begin again

Other information

- see hair loss pictures on side of this carton
- before use, read all information on carton and enclosed leaflet
- keep the carton. It contains important information.
- in clinical studies of mostly white women aged 18 to 45 years with mild to moderate degrees of hair loss, the following response to 2% minoxidil topical solution was reported: 19% of women reported moderate hair regrowth after using 2% minoxidil topical solution for 8 months (19% had moderate regrowth; 40% had minimal regrowth). This compares with 7% of women reporting moderate hair regrowth after using the placebo, the liquid without minoxidil in it, for 8 months (7% had moderate regrowth; 33% had minimal regrowth).
- store at controlled room temperature 20° to 25°C (68° to 77°F).

Inactive ingredients

alcohol (60% v/v), propylene glycol, purified water

Questions?

Call 1-877-753-3935 Monday-Friday 9AM-5PM EST

Principal display panel

Compare to the active ingredient in Women's Rogaine®††

Minoxidal Topical Solution, USP 2%

HAIR REGROWTH TREATMENT

For Women

Topical Solution Unscented

- Reactivates hair follicles to stimulate regrowth
- Clinically proven to help regrow hair
- For best results, apply directly to scalp twice daily

mL (FL OZ) BOTTLE

††This product is not affiliated with, manufactured by, or produced by the makers or owners of Rogaine®.

DISTRIBUTED BY: WALGREEN CO.

DEERFIELD, IL 60015

Package label

WALGREENS Hair Regrowth Treatment